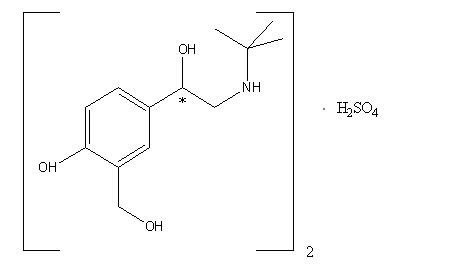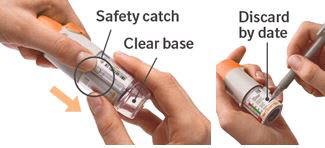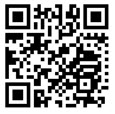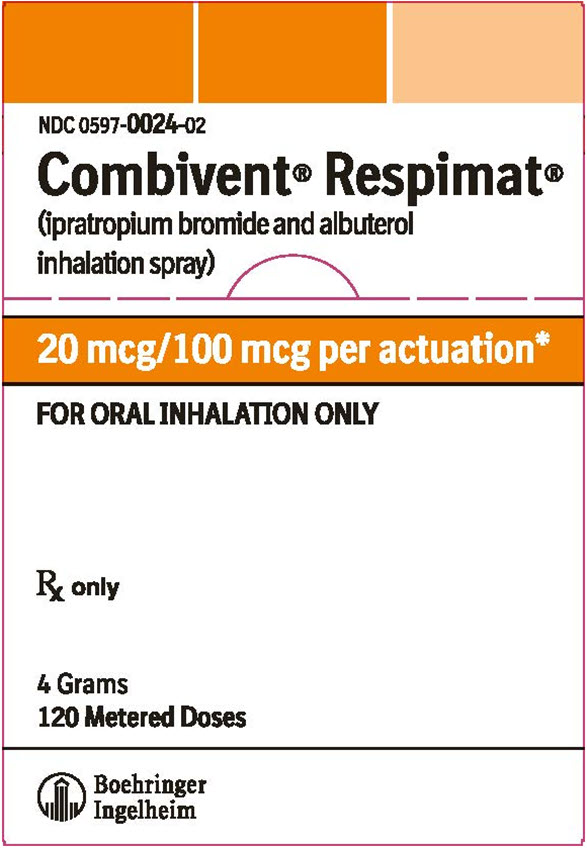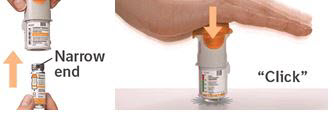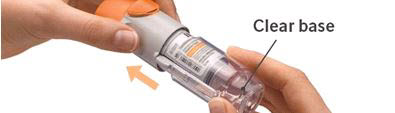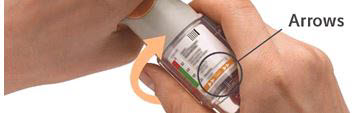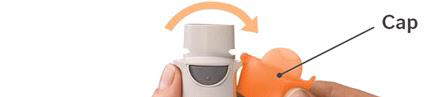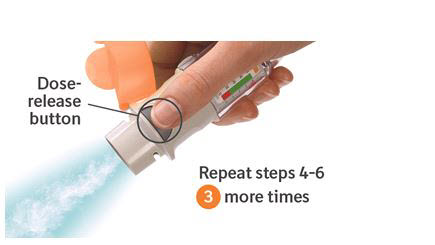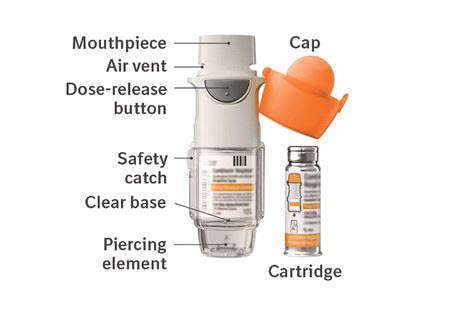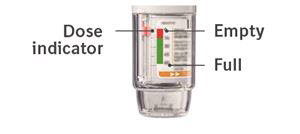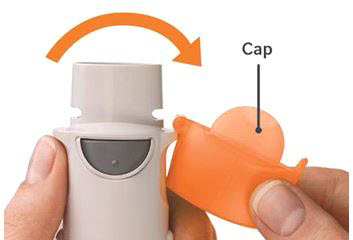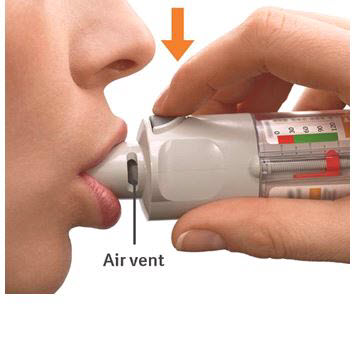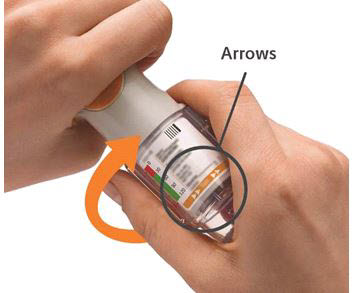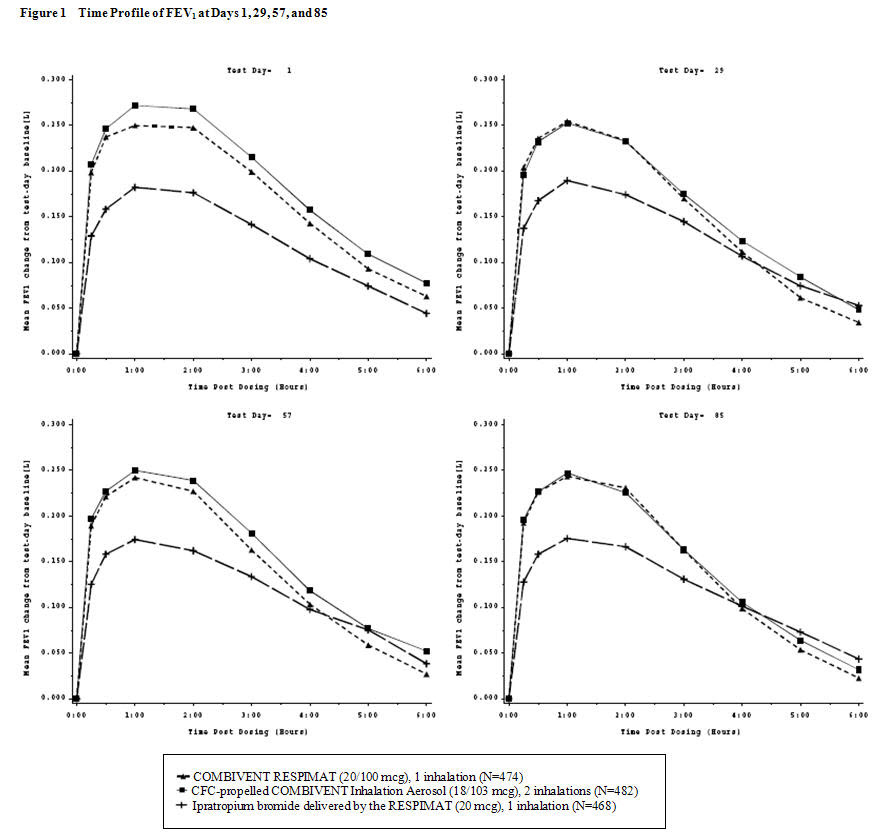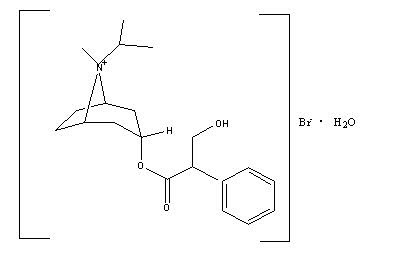 DRUG LABEL: Combivent Respimat
NDC: 0597-0024 | Form: SPRAY, METERED
Manufacturer: Boehringer Ingelheim Pharmaceuticals, Inc.
Category: prescription | Type: HUMAN PRESCRIPTION DRUG LABEL
Date: 20251201

ACTIVE INGREDIENTS: IPRATROPIUM BROMIDE 20 ug/1 1; ALBUTEROL SULFATE 100 ug/1 1

HIGHLIGHTS OF PRESCRIBING INFORMATION

These highlights do not include all the information needed to use COMBIVENT RESPIMAT safely and effectively. See full prescribing information for COMBIVENT RESPIMAT.
COMBIVENT® RESPIMAT® (ipratropium bromide and albuterol inhalation spray), for oral inhalation use
Initial U.S. Approval: 1996

1 INDICATIONS AND USAGE

COMBIVENT RESPIMAT Inhalation Spray is a combination of ipratropium bromide (an anticholinergic agent) and albuterol sulfate (a beta2‑adrenergic agonist) indicated for:

- Patients with chronic obstructive pulmonary disease (COPD) on a regular aerosol bronchodilator who continue to have evidence of bronchospasm and who require a second bronchodilator (1)

2 DOSAGE AND ADMINISTRATION

For oral inhalation only

- One inhalation four times a day, not to exceed six inhalations in 24 hours (2)

3 DOSAGE FORMS AND STRENGTHS

- Inhalation spray: 20 mcg ipratropium bromide (monohydrate) and 100 mcg albuterol (equivalent to 120 mcg albuterol sulfate) per actuation with the COMBIVENT RESPIMAT inhaler (3)

4 CONTRAINDICATIONS

- Hypersensitivity to any of the ingredients in COMBIVENT RESPIMAT (4)
- Hypersensitivity to atropine or any of its derivatives (4)

5 WARNINGS AND PRECAUTIONS

- Paradoxical bronchospasm: Discontinue COMBIVENT RESPIMAT immediately and treat with alternative therapy if paradoxical bronchospasm occurs (5.1)
- Patients with cardiovascular system disorders: Use with caution because of beta-adrenergic stimulation (5.2)
- Ocular effects: Advise patients to avoid spraying into eyes and to contact a physician if blurred vision, halos, or other visual disturbances occur. Monitor patients with narrow-angle glaucoma. (5.3)
- Urinary retention: Use with caution in patients with prostatic hyperplasia or bladder-neck obstruction (5.4)
- Hypersensitivity reactions including anaphylaxis: Discontinue COMBIVENT RESPIMAT and institute alternative therapy if immediate hypersensitivity reactions such as urticaria, angioedema, rash, bronchospasm, anaphylaxis, or oropharyngeal edema occur (5.6)
- Coexisting conditions: Use with caution in patients with convulsive disorders, hyperthyroidism, or diabetes mellitus (5.7)

6 ADVERSE REACTIONS

Most common (≥2%) adverse reactions for COMBIVENT RESPIMAT (20/100 mcg) are upper respiratory infection, nasopharyngitis, cough, bronchitis, headache, and dyspnea (6.1)

To report SUSPECTED ADVERSE REACTIONS, contact Boehringer Ingelheim Pharmaceuticals, Inc. at 1-800-542-6257 or FDA at 1-800-FDA-1088 or www.fda.gov/medwatch.

7 DRUG INTERACTIONS

- Anticholinergics: May interact additively with concomitantly used anticholinergic medications. Avoid administration of COMBIVENT RESPIMAT with other anticholinergic-containing drugs (7.1)
- Beta-adrenergic agonists: May increase the risk of adverse cardiovascular effects. Avoid coadministration of COMBIVENT RESPIMAT and other sympathomimetic agents (7.2)
- Beta-blockers: Inhibit the effect of albuterol. Consider alternative therapy in patients with hyperreactive airways (7.3)
- Diuretics: Electrocardiographic changes and/or hypokalemia associated with diuretics may worsen with concomitant use of beta-agonists. Consider monitoring potassium levels. (7.4)
- Monoamine oxidase inhibitors (MAOs) or tricyclic antidepressants: May potentiate effect of albuterol on the vascular system. Consider alternative therapy in patients taking MAOs or tricyclic antidepressants. (7.5)

FULL PRESCRIBING INFORMATION

1 INDICATIONS AND USAGE

COMBIVENT RESPIMAT is a combination of ipratropium bromide (an anticholinergic agent) and albuterol sulfate (a beta2-adrenergic agonist) indicated for use in patients with chronic obstructive pulmonary disease (COPD) on a regular aerosol bronchodilator who continue to have evidence of bronchospasm and who require a second bronchodilator.

2 DOSAGE AND ADMINISTRATION

The recommended dosage of COMBIVENT RESPIMAT is one inhalation four times a day. Patients may take additional inhalations as required; however, the total number of inhalations should not exceed six in 24 hours.

Prior to first use, the COMBIVENT RESPIMAT cartridge is inserted into the COMBIVENT RESPIMAT inhaler and the unit is primed. When using the unit for the first time, patients are to actuate the inhaler toward the ground until an aerosol cloud is visible and then repeat the process three more times. The unit is then considered primed and ready for use. If not used for more than 3 days, patients are to actuate the inhaler once to prepare the inhaler for use. If not used for more than 21 days, patients are to actuate the inhaler until an aerosol cloud is visible and then repeat the process three more times to prepare the inhaler for use [see Patient Counseling Information (17)].

Safety and efficacy of additional doses of COMBIVENT RESPIMAT beyond six inhalations/24 hours have not been studied. Also, safety and efficacy of extra doses of ipratropium or albuterol in addition to the recommended doses of COMBIVENT RESPIMAT have not been studied.

3 DOSAGE FORMS AND STRENGTHS

COMBIVENT RESPIMAT consists of a COMBIVENT RESPIMAT inhaler and an aluminum cylinder (COMBIVENT RESPIMAT cartridge) containing a combination of ipratropium bromide (monohydrate) and albuterol sulfate. The COMBIVENT RESPIMAT cartridge is only intended for use with the COMBIVENT RESPIMAT inhaler.

Each actuation from the COMBIVENT RESPIMAT inhaler delivers 20 mcg ipratropium bromide (monohydrate) and 100 mcg albuterol (equivalent to 120 mcg albuterol sulfate) from the mouthpiece.

4 CONTRAINDICATIONS

COMBIVENT RESPIMAT is contraindicated in the following conditions [see Warnings and Precautions (5.6)]:

- Hypersensitivity to any of the ingredients in COMBIVENT RESPIMAT
- Hypersensitivity to atropine or any of its derivatives

5 WARNINGS AND PRECAUTIONS

5.1 Paradoxical Bronchospasm

COMBIVENT RESPIMAT can produce paradoxical bronchospasm that can be life-threatening. If it occurs, therapy with COMBIVENT RESPIMAT should be discontinued immediately and alternative therapy instituted.

5.2 Cardiovascular Effects

The albuterol sulfate contained in COMBIVENT RESPIMAT, like other beta‑adrenergic agonists, can produce a clinically significant cardiovascular effect in some patients, as measured by pulse rate, blood pressure, and/or symptoms. If these symptoms occur, COMBIVENT RESPIMAT may need to be discontinued. There is some evidence from postmarketing data and published literature of rare occurrences of myocardial ischemia associated with albuterol. In addition, beta‑adrenergic agonists have been reported to produce electrocardiogram (ECG) changes, such as flattening of the T wave, prolongation of the QTc interval, and ST segment depression. Therefore, COMBIVENT RESPIMAT should be used with caution in patients with cardiovascular disorders, especially coronary insufficiency, cardiac arrhythmias, and hypertension [see Drug Interactions (7.2)].

5.3 Ocular Effects

Ipratropium bromide, a component of COMBIVENT RESPIMAT, is an anticholinergic and may increase intraocular pressure. This may result in precipitation or worsening of narrow-angle glaucoma. Therefore, COMBIVENT RESPIMAT should be used with caution in patients with narrow-angle glaucoma [see Drug Interactions (7.1)].

Patients should avoid spraying COMBIVENT RESPIMAT into the eyes. If a patient sprays COMBIVENT RESPIMAT into their eyes they may cause acute eye pain or discomfort, temporary blurring of vision, mydriasis, visual halos, or colored images in association with red eyes from conjunctival or corneal congestion. Advise patients to consult their physician immediately if any of these symptoms develop while using COMBIVENT RESPIMAT.

5.4 Urinary Retention

Ipratropium bromide, a component of COMBIVENT RESPIMAT, is an anticholinergic and may cause urinary retention. Therefore, caution is advised when administering this medication to patients with prostatic hyperplasia or bladder-neck obstruction [see Drug Interactions (7.1)].

5.5 Do Not Exceed Recommended Dosage

Fatalities have been reported in association with excessive use of inhaled sympathomimetic drugs in patients with asthma. The exact cause of death is unknown, but cardiac arrest following an unexpected development of a severe acute asthmatic crisis and subsequent hypoxia is suspected [see Drug Interactions (7.2)].

5.6 Hypersensitivity Reactions Including Anaphylaxis

Hypersensitivity reactions including urticaria, angioedema, rash, bronchospasm, anaphylaxis, and oropharyngeal edema may occur after administration of ipratropium bromide or albuterol sulfate. In clinical trials and postmarketing experience with ipratropium containing products, hypersensitivity reactions such as skin rash, pruritus, angioedema of tongue, lips and face, urticaria (including giant urticaria), laryngospasm, and anaphylactic reactions have been reported [see Adverse Reactions (6.1, 6.2)]. If such a reaction occurs, therapy with COMBIVENT RESPIMAT should be stopped at once and alternative treatment should be considered [see Contraindications (4)].

5.7 Coexisting Conditions

COMBIVENT RESPIMAT contains albuterol sulfate, a beta2-adrenergic sympathomimetic amine and, therefore, should be used with caution in patients with convulsive disorders, hyperthyroidism, or diabetes mellitus, and in patients who are unusually responsive to sympathomimetic amines.

5.8 Hypokalemia

Beta2‑adrenergic agonists may produce significant hypokalemia in some patients (possibly through intracellular shunting) which has the potential to produce adverse cardiovascular effects. The decrease in serum potassium is usually transient, not requiring supplementation [see Drug Interactions (7.2)].

6 ADVERSE REACTIONS

Use of albuterol, a beta2-adrenergic agonist, may be associated with the following:

- Paradoxical bronchospasm [see Warnings and Precautions (5.1)]
- Cardiovascular effects [see Warnings and Precautions (5.2)]
- Hypersensitivity reactions including anaphylaxis [see Contraindications (4) and Warnings and Precautions (5.6)]
- Hypokalemia [see Warnings and Precautions (5.8)]

Albuterol is a component of COMBIVENT RESPIMAT.

Use of ipratropium bromide, an anticholinergic, may result in the following:

- Ocular effects [see Warnings and Precautions (5.3)]
- Urinary retention [see Warnings and Precautions (5.4)]

Ipratropium bromide is a component of COMBIVENT RESPIMAT.

6.1 Clinical Trials Experience

COMBIVENT RESPIMAT 12-Week Clinical Trials

The safety data described in Table 1 below are derived from one 12-week, randomized, multicenter, double-blind, double-dummy, parallel-group trial that compared COMBIVENT RESPIMAT (20/100 mcg), CFC-propelled COMBIVENT Inhalation Aerosol (36/206 mcg), and ipratropium bromide delivered by the RESPIMAT inhaler (20 mcg) administered four times a day in 1,460 adult COPD patients (955 males and 505 females) 40 years of age and older. Of these patients, 486 were treated with COMBIVENT RESPIMAT. The COMBIVENT RESPIMAT group was composed of mostly Caucasian (88.5%) patients with a mean age of 63.8 years, and a mean percent predicted FEV1 at screening of 41.5%. Patients with narrow-angle glaucoma, symptomatic prostatic hypertrophy or bladder-neck obstruction were excluded from the trial.

Because clinical trials are conducted under widely varying conditions, adverse reaction rates observed in the clinical trials of a drug cannot be directly compared to rates in the clinical trials of another drug and may not reflect the rates observed in practice.

Table 1 shows all adverse reactions that occurred with a frequency of ≥2% in the COMBIVENT RESPIMAT treatment group in the 12-week COPD trial. The frequency of the corresponding adverse reactions in the CFC-propelled COMBIVENT Inhalation Aerosol and ipratropium bromide delivered by the RESPIMAT inhaler groups is included for comparison. The rates are derived from all reported adverse reactions of that type not present at baseline, whether considered drug-related or not by the clinical investigator.

Table 1 Adverse Reactions in ≥2% of Patients in the COMBIVENT RESPIMAT Group in a 12-Week COPD Clinical Trial
Body System (Event) |  | 12-Week Ipratropium-Controlled Trial
 |  | COMBIVENT RESPIMAT (20/100 mcg) | CFC-propelled COMBIVENT Inhalation Aerosol (36/206 mcg) | Ipratropium bromide by the RESPIMAT Inhaler (20 mcg)
 |  | [n=486] | [n=491] | [n=483]
Patients with any adverse reaction |  | 46 | 52 | 45
Respiratory, thoracic, and mediastinal disorders
 | Cough Dyspnea | 3 2 | 2 2 | 2 3
Nervous system disorders
 | Headache | 3 | 2 | 3
Infections and infestations
 | Bronchitis Nasopharyngitis Upper Respiratory infection | 3 4 3 | 3 3 4 | 1 4 3

Adverse reactions that occurred in <2% in the COMBIVENT RESPIMAT (20/100 mcg) group observed in this 12-week trial include: Vascular disorders: hypertension; Nervous system disorders: dizziness and tremor; Musculoskeletal and connective tissue disorder: muscle spasms and myalgia; Gastrointestinal disorders: diarrhea, nausea, dry mouth, constipation, and vomiting; General disorders and administration site conditions: asthenia, influenza-like illness, and chest discomfort; Eye disorders: eye pain; Metabolism and nutritional disorders: hypokalemia; Cardiac disorders: palpitations and tachycardia; Skin and subcutaneous tissue disorders: pruritus and rash; Respiratory, thoracic, and mediastinal disorders; pharyngolaryngeal pain and wheezing.

A separate 12-week trial evaluated a higher than approved dosage of COMBIVENT RESPIMAT in 1,118 COPD patients. Patients were randomized to COMBIVENT RESPIMAT (40/200 mcg) (n=345), CFC-propelled COMBIVENT Inhalation Aerosol (36/206 mcg) (n=180), ipratropium delivered by the RESPIMAT (40 mcg) (n=252) or placebo (n=341). The overall incidence and nature of adverse reactions observed were similar to the adverse reactions seen with COMBIVENT RESPIMAT 20/100 mcg.

COMBIVENT RESPIMAT Long-Term (48-week) Safety Trial

Long-term chronic use safety data for COMBIVENT RESPIMAT were obtained from one 48-week, randomized, multicenter, open-label, parallel-group trial that compared COMBIVENT RESPIMAT (20/100 mcg), CFC-propelled COMBIVENT Inhalation Aerosol (36/206 mcg), and the free combination of ipratropium bromide (34 mcg) and albuterol (180 mcg) HFA inhalation aerosols administered 4 times a day in 465 adult COPD patients (273 males and 192 females) 40 years of age and older. Of these patients, 157 were treated with COMBIVENT RESPIMAT. The COMBIVENT RESPIMAT group was composed of mostly Caucasian (93.5%) patients with a mean age of 62.9 years, and a mean percent predicted FEV1 at screening of 47.0%. An evaluation of the safety data from the trial revealed that most adverse reactions were similar in type and rate between treatment groups. However, cough occurred more frequently in patients enrolled in the COMBIVENT RESPIMAT group (7.0%) compared to those in the CFC-propelled COMBIVENT Inhalation Aerosol (2.6%) or the free combination of ipratropium bromide and albuterol HFA inhalation aerosols (3.9%) groups.

In addition to the adverse reactions reported in the controlled clinical trial with COMBIVENT RESPIMAT, adverse reaction information concerning CFC-propelled COMBIVENT Inhalation Aerosol is derived from two 12-week controlled clinical trials (N=358 for CFC-propelled COMBIVENT Inhalation Aerosol). Adverse reactions reported in ≥2% of patients in the CFC-propelled COMBIVENT Inhalation Aerosol treatment group include: bronchitis, upper respiratory tract infection, headache, dyspnea, cough, pain, respiratory disorder, sinusitis, pharyngitis, and nausea. Adverse reactions reported in <2% of patients in the CFC-propelled COMBIVENT Inhalation Aerosol treatment group include: edema, fatigue, hypertension, dizziness, nervousness, tremor, dysphonia, insomnia, diarrhea, dry mouth, dyspepsia, vomiting, arrhythmia, palpitation, tachycardia, arthralgia, angina, increased sputum, taste perversion, urinary tract infection, dysuria, dry throat, and bronchospasm.

6.2 Postmarketing Experience

In addition to the adverse reactions reported during clinical trials, the following adverse reactions have been identified during post-approval use of CFC-propelled COMBIVENT Inhalation Aerosol. Since CFC-propelled COMBIVENT Inhalation Aerosol and COMBIVENT RESPIMAT contain the same active ingredients, one should take into account the fact that the adverse reactions seen with CFC-propelled COMBIVENT Inhalation Aerosol could also occur with COMBIVENT RESPIMAT. Because these events are reported voluntarily from a population of uncertain size, it is not always possible to reliably estimate their frequency or establish a causal relationship to drug exposure.

Eye disorders: glaucoma, blurred vision, mydriasis, conjunctival hyperemia, halo vision, accommodation disorder, ocular irritation, and corneal edema
Gastrointestinal disorders: gastrointestinal motility disorder, drying of secretions, stomatitis, and mouth edema
Immune system disorders: hypersensitivity
Investigations: intraocular pressure increased, blood pressure diastolic decreased, and blood pressure systolic increased
Musculoskeletal and connective tissue disorders: muscular weakness
Psychiatric disorders: CNS stimulation, mental disorder
Respiratory, thoracic, and mediastinal disorders: throat irritation, paradoxical bronchospasm, wheezing, nasal congestion, and pharyngeal edema
Skin and subcutaneous tissue disorders: angioedema, hyperhidrosis, and skin reaction
Urinary disorders: urinary retention
Cardiac disorders: myocardial ischemia

Allergic-type reactions such as skin reactions including rash, pruritus, and urticaria (including giant urticaria), angioedema including that of tongue, lips and face, laryngospasm, and anaphylactic reaction have also been reported with CFC-propelled COMBIVENT Inhalation Aerosol, with positive re-challenge in some cases [see Warnings and Precautions (5.6)].

In a 5-year placebo-controlled trial, hospitalizations for supraventricular tachycardia and/or atrial fibrillation occurred with an incidence rate of 0.5% in COPD patients receiving CFC-propelled ATROVENT® (ipratropium bromide) Inhalation Aerosol.

Metabolic acidosis has been reported with use of albuterol-containing products.

7 DRUG INTERACTIONS

COMBIVENT RESPIMAT has been used concomitantly with other drugs, including beta-adrenergic bronchodilators, methylxanthines, and oral and inhaled steroids, commonly used in the treatment of chronic obstructive pulmonary disease. There are no formal studies fully evaluating the interaction effects of COMBIVENT RESPIMAT and these drugs with respect to safety and effectiveness.

7.1 Anticholinergic Agents

There is the potential for an additive interaction with concomitantly used anticholinergic medications. Therefore, avoid coadministration of COMBIVENT RESPIMAT with other anticholinergic-containing drugs as this may lead to an increase in anticholinergic adverse effects [see Warnings and Precautions (5.3, 5.4)].

7.2 Beta‑adrenergic Agonists

Caution is advised in the coadministration of COMBIVENT RESPIMAT and other sympathomimetic agents due to the increased risk of adverse cardiovascular effects [see Warnings and Precautions (5.2, 5.5)].

7.3 Beta-receptor Blocking Agents

Beta-receptor blocking agents and albuterol inhibit the effect of each other. Beta-receptor blocking agents should be used with caution in patients with hyperreactive airways.

7.4 Diuretics

The ECG changes and/or hypokalemia which may result from the administration of non‑potassium sparing diuretics (such as loop or thiazide diuretics) can be acutely worsened by beta2-agonists, especially when the recommended dosage of the beta2-agonist is exceeded. Although the clinical significance of these effects is not known, caution is advised in the coadministration of beta-agonist‑containing drugs, such as COMBIVENT RESPIMAT, with non‑potassium sparing diuretics. Consider monitoring potassium levels.

7.5 Monoamine Oxidase Inhibitors or Tricyclic Antidepressants

COMBIVENT RESPIMAT should be administered with extreme caution to patients being treated with monoamine oxidase inhibitors or tricyclic antidepressants or within 2 weeks of discontinuation of such agents because the action of albuterol on the cardiovascular system may be potentiated. Consider alternative therapy in patients taking MAOs or tricyclic antidepressants [see Warnings and Precautions (5.2)].

8 USE IN SPECIFIC POPULATIONS

8.1 Pregnancy

Risk Summary

There are no randomized clinical studies of COMBIVENT RESPIMAT, or its individual components, ipratropium bromide and albuterol sulfate, in pregnant women. Ipratropium is negligibly absorbed systemically following oral inhalation; therefore, maternal use is not expected to result in fetal exposure to the drug [see Clinical Pharmacology (12.3)]. Published literature, including cohort studies, case control studies and case series, over several decades have not identified a drug-associated risk of major birth defects, miscarriage or adverse maternal or fetal outcomes with ipratropium bromide. Available data from published epidemiological studies and postmarketing case reports of pregnancy outcomes following inhaled albuterol use do not consistently demonstrate a risk of major birth defects or, miscarriage. There are clinical considerations with the use of COMBIVENT RESPIMAT in pregnant women [see Clinical Considerations]. Animal reproduction studies have not been conducted with COMBIVENT RESPIMAT, however, animal studies are available with its individual components, ipratropium bromide and albuterol sulfate.

Based on oral reproduction studies, no evidence of structural alterations was observed when ipratropium bromide was administered to pregnant mice, rats, and rabbits during organogenesis at doses approximately 340, 68,000 and 17,000 times, respectively, the maximum recommended human daily inhalation dose (MRHDID) in adults on a mg/m^2 basis.

When albuterol was administered to pregnant mice during organogenesis there was evidence of cleft palate at doses approximately equivalent to the maximum recommended human daily inhalation dose (MRHDID) [see Data].

The estimated background risk of major birth defects and miscarriage for the indicated population is unknown. All pregnancies have a background risk of birth defect, loss or other adverse outcomes. In the U.S. general population, the estimated risk of major birth defects and miscarriage in clinically recognized pregnancies is 2% to 4% and 15% to 20%, respectively.

Clinical Consideration

Labor or Delivery

Because of the potential for beta-agonist interference with uterine contractility, use of COMBIVENT RESPIMAT for the treatment of COPD during labor should be restricted to those patients in whom the benefits clearly outweigh the risk. Serious adverse reactions, including pulmonary edema, have been reported during or following treatment of premature labor with beta2-agonists, including albuterol.

Data

Animal Data

Ipratropium bromide

In animal reproduction studies, oral and inhalation administration of ipratropium bromide to pregnant mice, rats and rabbits during the period of organogenesis did not show evidence of fetal structural alterations. The ipratropium dose in oral studies in mice, rats, and rabbits was up to approximately 340, 68,000 and 17,000 times, respectively, the maximum recommended human daily inhalation dose (MRHDID) in adults (on a mg/m^2 basis at maternal doses in each species of 10, 1,000 and 125 mg/kg/day, respectively). The ipratropium dose in inhalation studies in rats and rabbits was up to approximately 100 and 240 times, respectively, the MRHDID in adults (on a mg/m^2 basis at maternal doses of 1.5 and 1.8 mg/kg/day, respectively). Embryotoxicity was observed as increased resorption in rats at oral doses approximately 6,100 times MRHDID in adults (on a mg/m^2 basis at maternal doses of 90 mg/kg/day and above). This effect is not considered relevant to human use due to the large doses at which it was observed and the difference in route of administration.

Albuterol

In a mouse reproduction study, subcutaneously administered albuterol sulfate produced cleft palate formation in 5 of 111 (4.5%) fetuses at a dose approximately equivalent to the MRHDID in adults (on a mg/m^2 basis at a maternal dose of 0.25 mg/kg/day) and in 10 of 108 (9.3%) fetuses at approximately 14 times the MRHDID in adults (on a mg/m^2 basis at a maternal dose of 2.5 mg/kg/day). Similar effects were not observed at approximately less than MRHDID in adults (on a mg/m^2 basis at a maternal dose of 0.025 mg/kg/day). Cleft palate also occurred in 22 of 72 (30.5%) fetuses from females treated with 2.5 mg/kg/day isoproterenol (positive control).

In a rabbit reproductive study, orally administered albuterol sulfate induced cranioschisis in 7 of 19 (37%) fetuses at approximately 1,100 times the MRHDID in adults (on a mg/m^2 basis at a maternal dose of 50 mg/kg/day).

In a rat reproduction study, an albuterol sulfate/HFA-134a formulation administered by inhalation did not produce any teratogenic effects at exposures approximately 80 times the MRHDID (on a mg/m^2 basis at a maternal dose of 10.5 mg/kg). A study in which pregnant rats were dosed with radiolabeled albuterol sulfate demonstrated that drug-related material is transferred from the maternal circulation to the fetus.

8.2 Lactation

Risk Summary

There are no available data on the presence of COMBIVENT RESPIMAT, or its components, ipratropium bromide or albuterol, in human milk, the effects on the breastfed infant, or the effects on milk production. Although lipid-insoluble quaternary cations pass into breast milk, ipratropium concentrations in plasma after inhaled therapeutic doses are low. Similarly, plasma levels of albuterol after inhaled therapeutic doses are low in humans. Therefore, ipratropium and albuterol concentrations in human breast milk are likely to be correspondingly low [see Clinical Pharmacology (12.3)]. The developmental and health benefits of breastfeeding should be considered along with the mother's clinical need for albuterol and any potential adverse effects on the breastfed child from albuterol or from the underlying maternal condition.

8.4 Pediatric Use

Safety and effectiveness of COMBIVENT RESPIMAT in pediatric patients have not been established. COMBIVENT RESPIMAT is indicated for use in patients with COPD on a regular aerosol bronchodilator who continue to have evidence of bronchospasm and who require a second bronchodilator. This disease does not normally occur in children.

8.5 Geriatric Use

In the 12-week trial in COPD, 48% of COMBIVENT RESPIMAT clinical trial patients were 65 years of age or over. In general, there were no marked differences between the proportion of patients with adverse reactions for the COMBIVENT RESPIMAT and CFC-propelled COMBIVENT Inhalation Aerosol treated patients. Cardiac and lower respiratory disorders occurred less frequently in the patients under the age of 65 and were balanced across treatment groups.

No overall differences in effectiveness were observed among treatment groups. Based on available data, no adjustment of COMBIVENT RESPIMAT dosage in geriatric patients is warranted.

10 OVERDOSAGE

The effects of overdosage are expected to be related primarily to albuterol sulfate. Acute overdosage with ipratropium bromide by inhalation is unlikely since ipratropium bromide is not well absorbed systemically after inhalation or oral administration. Manifestations of overdosage with albuterol may include anginal pain, hypertension, hypokalemia, tachycardia with rates up to 200 beats per minute, metabolic acidosis, and exaggeration of the pharmacologic effects listed in the Adverse Reactions section [see Adverse Reactions (6)]. As with all beta2-adrenergic agonist aerosol medications, cardiac arrest and even death may be associated with abuse.

Treatment of overdosage consists of discontinuation of COMBIVENT RESPIMAT together with institution of appropriate medical and supportive therapy. Dialysis is not appropriate treatment for overdosage of albuterol as an inhalation aerosol; the judicious use of a cardiovascular beta‑receptor blocker, such as metoprolol tartrate, may be indicated.

11 DESCRIPTION

COMBIVENT RESPIMAT is a combination of ipratropium bromide (monohydrate) and albuterol sulfate.

Ipratropium bromide is an anticholinergic bronchodilator chemically described as 8-azoniabicyclo[3.2.1] octane, 3-(3-hydroxy-1-oxo-2-phenylpropoxy)-8-methyl-8-(1-methylethyl)-, bromide monohydrate, (3-endo, 8-syn)-: a synthetic quaternary ammonium compound chemically related to atropine. Ipratropium bromide is a white to off-white crystalline substance, freely soluble in water and methanol, sparingly soluble in ethanol, and insoluble in lipophilic solvents such as ether, chloroform, and fluorocarbons.

The structural formula is:

C20H30BrNO3•H2O ipratropium bromide Mol. Wt. 430.4

Albuterol sulfate, chemically known as (1,3-benzenedimethanol, α'-[[(1,1dimethylethyl) amino] methyl]-4-hydroxy, sulfate (2:1)(salt), (±)- is a relatively selective beta2-adrenergic bronchodilator. Albuterol is the official generic name in the United States. The World Health Organization recommended name for the drug is salbutamol. Albuterol sulfate is a white to off-white crystalline powder, freely soluble in water and slightly soluble in alcohol, chloroform, and ether.

The structural formula is:

(C13H21NO3)2•H2SO4 albuterol sulfate Mol. Wt. 576.7

The drug product, COMBIVENT RESPIMAT, is composed of a sterile, aqueous solution of ipratropium bromide and albuterol sulfate filled into a 4.5 mL plastic container crimped into an aluminum cylinder (COMBIVENT RESPIMAT cartridge) for use with the COMBIVENT RESPIMAT inhaler. Excipients include benzalkonium chloride, edetate disodium, hydrochloric acid, and water for injection. The COMBIVENT RESPIMAT cartridge is only intended for use with the COMBIVENT RESPIMAT inhaler. The COMBIVENT RESPIMAT inhaler is a hand held, pocket sized oral inhalation device that uses mechanical energy to generate a slow-moving aerosol cloud of medication from a metered volume of the drug solution. The COMBIVENT RESPIMAT inhaler has an orange-colored cap.

When used with the COMBIVENT RESPIMAT inhaler, each cartridge containing 4 grams of a sterile aqueous solution delivers the labeled number of metered actuations after preparation for use. Each actuation from the COMBIVENT RESPIMAT inhaler delivers 20 mcg ipratropium bromide (monohydrate) and 100 mcg albuterol (equivalent to 120 mcg albuterol sulfate) in 11.4 mcL of solution from the mouthpiece. As with all inhaled drugs, the actual amount of drug delivered to the lung may depend on patient factors, such as the coordination between the actuation of the inhaler and inspiration through the delivery system. The duration of inspiration should be at least as long as the spray duration (1.5 seconds).

Prior to first use, the COMBIVENT RESPIMAT cartridge is inserted into the COMBIVENT RESPIMAT inhaler and the unit is primed. When using the unit for the first time, patients are to actuate the inhaler toward the ground until an aerosol cloud is visible and then repeat the process three more times. The unit is then considered primed and ready for use. If not used for more than 3 days, patients are to actuate the inhaler once to prepare the inhaler for use. If not used for more than 21 days, patients are to actuate the inhaler until an aerosol cloud is visible and then repeat the process three more times to prepare the inhaler for use [see Patient Counseling Information (17)].

12 CLINICAL PHARMACOLOGY

12.1 Mechanism of Action

COMBIVENT RESPIMAT: COMBIVENT RESPIMAT is a combination of the anticholinergic ipratropium bromide and the beta2-adrenergic agonist albuterol sulfate. The mechanisms of action described below for the individual components apply to COMBIVENT RESPIMAT. The two classes of medications (an anticholinergic and a beta2-adrenergic agonist) are both bronchodilators. Simultaneous administration of both an anticholinergic (ipratropium bromide) and a beta2-sympathomimetic (albuterol sulfate) is designed to produce a greater bronchodilator effect than when either drug is utilized alone at its recommended dosage. The efficacy of COMBIVENT RESPIMAT is likely to be due to a local effect on the muscarinic and beta2-adrenergic receptors in the lung.

Ipratropium bromide

Ipratropium bromide is an anticholinergic (parasympatholytic) agent which, based on animal studies, appears to inhibit vagally mediated reflexes by antagonizing the action of acetylcholine, the transmitter agent released at the neuromuscular junctions in the lung. Anticholinergics prevent the increases in intracellular concentration of Ca++ which is caused by interaction of acetylcholine with the muscarinic receptors on bronchial smooth muscle.

Albuterol sulfate

In vitro studies and in vivo pharmacology studies have demonstrated that albuterol has a preferential effect on beta2-adrenergic receptors compared with isoproterenol. While it is recognized that beta2-adrenergic receptors are the predominant receptors on bronchial smooth muscle, recent data indicate that there is a population of beta2-receptors in the human heart which comprise between 10% and 50% of cardiac beta-adrenergic receptors. The precise function of these receptors, however, is not yet established [see Warnings and Precautions (5.2)].

Activation of beta2-adrenergic receptors on airway smooth muscle leads to the activation of adenylyl cyclase and to an increase in the intracellular concentration of cyclic-3',5'-adenosine monophosphate (cyclic AMP). This increase of cyclic AMP leads to the activation of protein kinase, which inhibits the phosphorylation of myosin and lowers intracellular ionic calcium concentrations, resulting in relaxation. Albuterol relaxes the smooth muscles of all airways, from the trachea to the terminal bronchioles. Albuterol acts as a functional antagonist to relax the airway irrespective of the spasmogen involved, thus protecting against all bronchoconstrictor challenges. Increased cyclic AMP concentrations are also associated with the inhibition of release of mediators from mast cells in the airway.

Albuterol has been shown in most clinical trials to have more bronchial smooth muscle relaxation effect than isoproterenol at comparable doses while producing fewer cardiovascular effects. However, all beta‑adrenergic agonist drugs, including albuterol sulfate, can produce a significant cardiovascular effect in some patients [see Warnings and Precautions (5.2)].

12.2 Pharmacodynamics

Ipratropium bromide

Cardiovascular effects
At recommended dosages, ipratropium bromide does not produce clinically significant changes in pulse rate or blood pressure.

Ocular effects
In studies without a positive control, ipratropium bromide did not alter pupil size, accommodation, or visual acuity.

Mucociliary clearance and respiratory secretions
Controlled clinical studies have demonstrated that ipratropium bromide does not alter either mucociliary clearance or the volume or viscosity of respiratory secretions.

Albuterol sulfate

Cardiovascular effects
Controlled clinical trials and other clinical experience have shown that inhaled albuterol, like other beta-adrenergic agonist drugs, can produce a significant cardiovascular effect in some patients, as measured by pulse rate, blood pressure, symptoms, and/or electrocardiographic changes.

12.3 Pharmacokinetics

Ipratropium bromide

Ipratropium bromide is a quaternary amine and hence, it is not readily absorbed into the systemic circulation either from the surface of the lung or from the gastrointestinal tract as confirmed by blood level and renal excretion studies.

The half-life of elimination is about 2 hours after inhalation or intravenous administration. Ipratropium bromide is minimally bound (0% to 9% in vitro) to plasma albumin and α1-acid glycoprotein. It is partially metabolized to inactive ester hydrolysis products. Following intravenous administration, approximately one-half of the dose is excreted unchanged in the urine.

Albuterol sulfate

Albuterol is longer acting than isoproterenol in most patients because it is not a substrate for the cellular uptake processes for catecholamines, nor for metabolism by catechol-O-methyl transferase. Instead, the drug is conjugatively metabolized to albuterol 4'-O-sulfate.

Intravenous pharmacokinetics of albuterol was studied in a comparable group of 16 healthy male volunteers; the mean terminal half-life following a 30-minute infusion of 1.5 mg was 3.9 hours, with a mean clearance of 439 mL/min/1.73 m^2.

COMBIVENT RESPIMAT Inhalation Spray

In a 12-week randomized, multicenter, double-blind, double-dummy parallel group trial, 108 US patients with COPD receiving either COMBIVENT RESPIMAT (20/100 mcg) or CFC-propelled COMBIVENT Inhalation Aerosol (36/206 mcg) four times daily participated in pharmacokinetic evaluations. Plasma ipratropium concentrations were low with an average peak plasma concentration of 33.5 pg/mL from COMBIVENT RESPIMAT. The majority of the study participants exhibited levels below the lower limit of quantitation (<10 pg/mL) by 4 to 6 hours following dosing. The steady state systemic exposure obtained for ipratropium bromide following COMBIVENT RESPIMAT was comparable to that of CFC-propelled COMBIVENT Inhalation Aerosol. Ipratropium plasma AUC and total amount of drug excreted unchanged in urine (Ae) ratios for COMBIVENT RESPIMAT/CFC-propelled COMBIVENT Inhalation Aerosol were 1.04 and 1.18, respectively. For albuterol the steady state systemic exposure was less from COMBIVENT RESPIMAT compared to that of CFC-propelled COMBIVENT Inhalation Aerosol. Albuterol plasma AUC and urine Ae ratios for COMBIVENT RESPIMAT/CFC-propelled COMBIVENT Inhalation Aerosol were 0.74 and 0.86, respectively.

Pharmacokinetic drug-drug interaction between ipratropium bromide and albuterol sulfate was evaluated in a crossover study in 12 healthy male volunteers who received CFC-propelled COMBIVENT Inhalation Aerosol and the two active components separately as individual treatments. Results from this study indicated that the coadministration of these two components from a single canister did not significantly alter the systemic absorption of either component, indicating lack of any pharmacokinetic interaction between these two drugs.

Specific Populations

Age
Consistent with CFC-propelled COMBIVENT Inhalation Aerosol (36/206 mcg), patients receiving COMBIVENT RESPIMAT (20/100 mcg) aged 65 years and over had higher steady state systemic exposures than patients aged under 65 years for both ipratropium (AUC = 166 vs. 105 pg•hr/mL, Cmax = 38.5 vs. 30.1 pg/mL) and albuterol (AUC = 5.44 vs. 3.27 ng•hr/mL, Cmax = 1.19 vs. 0.74 ng/mL).

Gender
The AUC and Cmax values for ipratropium were 131 pg.hr/mL and 35.4 pg/mL in males and 123 pg.hr/mL and 31.7 pg/mL in females, respectively. The AUC- and Cmax-values for albuterol were 4.0 ng•hr/mL and 0.89 ng/mL in males and 4.2 ng•hr/mL and 0.93 ng/mL in females, respectively.

Hepatic and Renal Impairment
The pharmacokinetics of COMBIVENT RESPIMAT or ipratropium bromide has not been studied in patients with hepatic or renal insufficiency.

Drug-Drug Interactions
No specific pharmacokinetic studies were conducted to evaluate potential drug-drug interactions with other medications.

13 NONCLINICAL TOXICOLOGY

13.1 Carcinogenesis, Mutagenesis, Impairment of Fertility

Ipratropium bromide

Two-year oral carcinogenicity studies in rats and mice have revealed no carcinogenic activity at doses up to 6 mg/kg/day (approximately 400 and 200 times the maximum recommended human daily inhalation dose of ipratropium bromide (MRHDID) in adults on a mg/m^2 basis, respectively).

Results of various mutagenicity/clastogenicity studies (Ames test, mouse dominant lethal test, mouse micronucleus test, and chromosome aberration of bone marrow in Chinese hamsters) were negative.

Fertility of male or female rats at oral doses up to 50 mg/kg/day (approximately 3,400 times the MRHDID in adults on a mg/m^2 basis) was unaffected by ipratropium bromide administration. At an oral dose of 500 mg/kg/day (approximately 34,000 times the MRHDID in adults on a mg/m^2 basis), ipratropium bromide produced a decrease in the conception rate.

Albuterol

Like other agents in its class, albuterol caused a significant dose-related increase in the incidence of benign leiomyomas of the mesovarium in a 2-year study in the rat at dietary doses of 2, 10, and 50 mg/kg/day (approximately 20, 110, and 560 times the MRHDID on a mg/m^2 basis). In another study this effect was blocked by the coadministration of propranolol. The relevance of these findings to humans is not known. An 18-month study in mice at dietary doses up to 500 mg/kg/day (approximately 2,800 times the MRHDID on a mg/m^2 basis) and a 99-week study in hamsters at oral doses up to 50 mg/kg/day (approximately 470 times the MRHDID on a mg/m^2 basis) revealed no evidence of tumorigenicity. Studies with albuterol revealed no evidence of mutagenesis.

Reproduction studies in rats with albuterol sulfate revealed no evidence of impaired fertility.

13.2 Animal Toxicology and/or Pharmacology

Preclinical: Intravenous studies in rats with albuterol sulfate have demonstrated that albuterol crosses the blood-brain barrier and reaches brain concentrations amounting to approximately 5% of the plasma concentrations. In structures outside the blood-brain barrier (pineal and pituitary glands), albuterol concentrations were found to be 100 times those in the whole brain.

Studies in laboratory animals (minipigs, rodents, and dogs) have demonstrated the occurrence of cardiac arrhythmias and sudden death (with histologic evidence of myocardial necrosis) when beta-agonists and methylxanthines were administered concurrently. The clinical significance of these findings is unknown.

14 CLINICAL STUDIES

The efficacy of COMBIVENT RESPIMAT (20/100 mcg) was evaluated in COPD patients in one randomized, double-blind, double-dummy parallel group trial. This was a 12-week trial in a total of 1,460 adult patients (955 males and 505 females) conducted to demonstrate the efficacy and safety of COMBIVENT RESPIMAT (20/100 mcg) in COPD. All patients were required to have a clinical diagnosis of COPD, be at least 40 years of age or older, to have an FEV1 of less than or equal to 65% predicted and an FEV1/FVC ratio of less than or equal to 0.7 at screening, and a smoking history of greater than 10 pack-years prior to entering the trial. Patients with narrow-angle glaucoma, symptomatic prostatic hypertrophy, or bladder neck obstruction were excluded from the trial. The majority of the patients (89%) were Caucasian, had a mean age of 64 years, a mean percent predicted pre-bronchodilator FEV1 of 41% and FEV1/FVC ratio of 0.45. The patients were randomized to one of the following active treatments COMBIVENT RESPIMAT (20/100 mcg) (n=486), CFC-propelled COMBIVENT Inhalation Aerosol (36/206 mcg) (n=491), and ipratropium bromide delivered by the RESPIMAT (20 mcg) (n=483) administered four times a day. Data from 1,424 patients were used in the efficacy analyses.

There were three primary efficacy variables: (i) Mean FEV1 over 0 to 6 hours post-dose defined as the AUC of the change from test-day baseline in FEV1 over 0 to 6 hours post-dose divided by 6 hours (FEV1 AUC0-6h); (ii) Mean FEV1 over 0 to 4 hours post-dose defined as the AUC of the change from test-day baseline in FEV1 over 0 to 4 hours post-dose divided by 4 hours (FEV1 AUC0-4h), and (iii) Mean FEV1 over 4 to 6 hours post-dose defined as the AUC of the change from test-day baseline in FEV1 over 4 to 6 hours post-dose divided by 2 hours (FEV1 AUC4-6h). Test-day baseline was the FEV1 recorded prior to inhaling the dose of randomized treatment on test day.

The three primary efficacy comparisons were: (i) Non-inferiority of COMBIVENT RESPIMAT (20/100 mcg) to CFC-propelled COMBIVENT Inhalation Aerosol (36/206 mcg) for the FEV1 AUC0-6h on Test Day 85; (ii) Superiority of COMBIVENT RESPIMAT (20/100 mcg) to ipratropium RESPIMAT (20 mcg) for the FEV1 AUC0-4h on Test Day 85, to demonstrate the contribution of albuterol in the combination product, and (iii) Non-inferiority of COMBIVENT RESPIMAT (20/100 mcg) in comparison to ipratropium RESPIMAT (20 mcg) for FEV1 AUC4-6h on Test Day 85, to demonstrate the contribution of ipratropium in the combination product. Non-inferiority was declared if the lower bound of the 95% confidence interval for the point estimate for the difference of COMBIVENT RESPIMAT minus the comparator was more than -50 mL.

COMBIVENT RESPIMAT (20/100 mcg) was shown to be non-inferior to CFC-propelled COMBIVENT Inhalation Aerosol (36/206 mcg) in terms of mean FEV1 AUC0-6h. The LS mean (mL) (95% CI) of the treatment difference was -3 (-22, 15). The FEV1 AUC0-4h for COMBIVENT RESPIMAT (20/100 mcg), was superior to that of ipratropium bromide [LS mean (mL) (95% CI) of the treatment difference was 47 mL (28, 66)] and the mean FEV1 AUC4-6h for COMBIVENT RESPIMAT (20/100 mcg) was non-inferior to that of ipratropium bromide [LS mean (mL) (95% CI) of the treatment difference was -17 (-39, 5)]. The FEV1 results on Test Days 1, 29, 57, and 85 are shown in Figure 1.

In this trial, COMBIVENT RESPIMAT (20/100 mcg) was shown to be clinically comparable (statistically non-inferior) to CFC-propelled COMBIVENT Inhalation Aerosol (36/206 mcg).

Additionally, in this trial, no differences in these efficacy comparisons were identified in males and females or in patients over 65 years of age versus those under 65 years of age. There were too few African-American subjects to adequately assess differences in effects in that population.

The median time to onset of bronchodilation, defined as an FEV1 increase of 15% or greater from test-day baseline, for the COMBIVENT RESPIMAT (20/100 mcg) group occurred at 13 minutes post-dose on Day 1.

The means are adjusted for treatment baseline and investigator site. A separate ANCOVA was fitted for each time point.
The imputation method for data missing because the patient withdrew from the trial was Last Visit Carried Forward.
The imputation method for data missing at the end of test days depends on why the data were missing.

A second study was conducted in 1,118 COPD patients using a higher than approved dosage of COMBIVENT RESPIMAT. Patients were randomized to COMBIVENT RESPIMAT (40/200 mcg) (n=345), CFC-propelled COMBIVENT Inhalation Aerosol (36/206 mcg) (n=180), ipratropium delivered by the RESPIMAT (40 mcg) (n=252) or placebo (n= 341). The study was supportive, particularly for safety [see Adverse Reactions (6.1)].

16 HOW SUPPLIED/STORAGE AND HANDLING

COMBIVENT RESPIMAT Inhalation Spray is supplied in a carton containing one COMBIVENT RESPIMAT cartridge and one COMBIVENT RESPIMAT inhaler.

The COMBIVENT RESPIMAT cartridge is provided as an aluminum cylinder with a tamper protection seal on the cap. The COMBIVENT RESPIMAT cartridge is only intended for use with the COMBIVENT RESPIMAT inhaler.

The COMBIVENT RESPIMAT inhaler is a cylindrical shaped plastic inhalation device with a gray colored body and a clear base. The clear base is removed to insert the cartridge. The inhaler contains a dose indicator. The orange-colored cap and the written information on the label of the gray inhaler body indicate that it is labeled for use with the COMBIVENT RESPIMAT cartridge.

COMBIVENT RESPIMAT Inhalation Spray is available as:
COMBIVENT RESPIMAT Inhalation Spray: 120 metered actuations (NDC 0597-0024-02)

The COMBIVENT RESPIMAT cartridge has a net fill weight of 4 grams and when used with the COMBIVENT RESPIMAT inhaler, is designed to deliver the labeled number of metered actuations after preparation for use. Each actuation from the COMBIVENT RESPIMAT inhaler delivers 20 mcg ipratropium bromide (monohydrate) and 100 mcg albuterol (equivalent to 120 mcg albuterol sulfate) from the mouthpiece.

When the labeled number of metered actuations has been dispensed from the inhaler, the RESPIMAT locking mechanism will be engaged and no more actuations can be dispensed.

After assembly, the COMBIVENT RESPIMAT inhaler should be discarded at the latest 3 months after first use or when the locking mechanism is engaged, whichever comes first.

Keep out of reach of children. Do not spray into eyes.

Storage

Store at 20°C to 25°C (68°F to 77°F); excursions permitted to 15°C to 30°C (59°F to 86°F) [see USP Controlled Room Temperature]. Avoid freezing.

17 PATIENT COUNSELING INFORMATION

Advise the patient to read the FDA-approved patient labeling (Instructions for Use).

Paradoxical Bronchospasm

Inform patients that COMBIVENT RESPIMAT can produce paradoxical bronchospasm that can be life-threatening. If paradoxical bronchospasm occurs, patients should discontinue using COMBIVENT RESPIMAT.

Ocular Effects

Caution patients to avoid spraying the aerosol into their eyes and advise that this may result in precipitation or worsening of narrow‑angle glaucoma, mydriasis, increased intraocular pressure, acute eye pain or discomfort, temporary blurring of vision, visual halos or colored images in association with red eyes from conjunctival and corneal congestion. Patients should also be advised that should any combination of these symptoms develop, they should consult their physician immediately.

Since dizziness, accommodation disorder, mydriasis, and blurred vision may occur with use of COMBIVENT RESPIMAT, patients should be cautioned about engaging in activities requiring balance and visual acuity such as driving a car or operating appliances or machinery.

Urinary Retention

Inform patients that COMBIVENT RESPIMAT may cause urinary retention and advise them to consult their physician if they experience difficulty with urination.

Adverse Effects Associated with Beta2-agonists

Inform patients of adverse effects associated with beta2-agonists, such as palpitations, chest pain, rapid heart rate, tremor, or nervousness [see Warnings and Precautions (5.2, 5.5)].

Frequency of Use

The action of COMBIVENT RESPIMAT should last 4 to 5 hours or longer. COMBIVENT RESPIMAT should not be used more frequently than recommended. Safety and efficacy of additional doses of COMBIVENT RESPIMAT beyond six inhalations in 24 hours have not been studied. Patients should be told not to increase the dose or frequency of COMBIVENT RESPIMAT without consulting a physician. Patients should be instructed that if they find that treatment with COMBIVENT RESPIMAT becomes less effective for symptomatic relief, their symptoms become worse, and/or they need to use the product more frequently than usual, medical attention should be sought immediately [see Warnings and Precautions (5.5)].

Hypersensitivity Reactions

Inform patients that hypersensitivity reactions, including urticaria, angioedema, rash, bronchospasm, anaphylaxis, and oropharyngeal edema, may occur after the administration of COMBIVENT RESPIMAT. Advise patients to immediately discontinue COMBIVENT RESPIMAT and consult a physician [see Warnings and Precautions (5.6)].

Concomitant Drug Use

Remind patients that while taking COMBIVENT RESPIMAT, other inhaled drugs should be taken only as directed by a physician [see Drug Interactions (7.1)].

Pregnancy

Patients who are pregnant or nursing should contact their physician about the use of COMBIVENT RESPIMAT [see Use in Specific Populations (8.1, 8.2)].

Preparation for Use and Priming

Instruct patients that priming COMBIVENT RESPIMAT is essential to ensure appropriate content of the medication in each actuation.

When using the unit for the first time, the COMBIVENT RESPIMAT cartridge is inserted into the COMBIVENT RESPIMAT inhaler and the unit is primed. COMBIVENT RESPIMAT patients are to actuate the inhaler toward the ground until an aerosol cloud is visible and then repeat the process three more times. The unit is then considered primed and ready for use. If not used for more than 3 days, patients are to actuate the inhaler once to prepare the inhaler for use. If not used for more than 21 days, patients are to actuate the inhaler until an aerosol cloud is visible and then repeat the process three more times to prepare the inhaler for use.

Distributed by:
Boehringer Ingelheim Pharmaceuticals, Inc.
Ridgefield, CT 06877 USA

Licensed from:
Boehringer Ingelheim International GmbH

RESPIMAT® is a registered trademark of and used under license from Boehringer Ingelheim International GmbH

COMBIVENT® is a registered trademark of and used under license from Boehringer Ingelheim Pharmaceuticals, Inc.

Copyright © 2025 Boehringer Ingelheim International GmbH
ALL RIGHTS RESERVED

COL10574BB102025
SPL10595D

PATIENT INFORMATION

Instructions for Use
COMBIVENT® RESPIMAT® (COM beh vent - RES peh mat)
(ipratropium bromide and albuterol inhalation spray)

For Oral Inhalation Only
Do not spray COMBIVENT RESPIMAT into your eyes.

Read these Instructions for Use before you start using COMBIVENT RESPIMAT and each time you get a refill. There may be new information. This leaflet does not take the place of talking to your doctor about your medical condition or your treatment.

Use COMBIVENT RESPIMAT exactly as prescribed by your doctor. Do not change your dose or how often you use COMBIVENT RESPIMAT without talking with your doctor.

Tell your doctor about all of the medicines you take. COMBIVENT RESPIMAT may affect the way some medicines work and some other medicines may affect the way COMBIVENT RESPIMAT works. Do not use other inhaled medicines with COMBIVENT RESPIMAT without talking to your doctor.

The COMBIVENT RESPIMAT inhaler has a slow-moving mist that helps you inhale the medicine.

Do not turn the clear base before inserting the cartridge.

How to store your COMBIVENT RESPIMAT inhaler
- Store COMBIVENT RESPIMAT at room temperature 68°F to 77°F (20°C to 25°C).
- Do not freeze your COMBIVENT RESPIMAT cartridge and inhaler.
- If COMBIVENT RESPIMAT has not been used for more than 3 days, release 1 puff towards the ground.
- If COMBIVENT RESPIMAT has not been used for more than 21 days, repeat steps 4 to 6 under the “Prepare for first use” until a mist is visible. Then repeat steps 4 to 6 three more times.
- Keep your COMBIVENT RESPIMAT cartridge and inhaler out of the reach of children.

How to care for your COMBIVENT RESPIMAT inhaler

Clean the mouthpiece, including the metal part inside the mouthpiece, with a damp cloth or tissue only, at least once a week. Any minor discoloration in the mouthpiece does not affect your COMBIVENT RESPIMAT inhaler.

When to get a new COMBIVENT RESPIMAT inhaler

- Your inhaler contains 120 puffs (120 doses); or if you have a sample, your inhaler contains 60 puffs (60 doses) instead.

- The dose indicator shows approximately how much medicine is left.
- When the dose indicator enters the red area of the scale you need to get a refill; there is approximately medicine for 7 days left (if you have a sample, there is approximately medicine for 3 days left).
- When the dose indicator reaches the end of the red scale, your COMBIVENT RESPIMAT is empty and automatically locks. At this point, the clear base cannot be turned any further.
- Three months after insertion of cartridge, throw away the COMBIVENT RESPIMAT even if it has not been used, or when the inhaler is locked, or when it expires, whichever comes first.

Prepare for first use

1. Remove clear base

- Keep the cap closed.
- Press the safety catch while firmly pulling off the clear base with your other hand. Be careful not to touch the piercing element.
- Write the discard by date on the label (3 months from the date the cartridge is inserted).

2. Insert cartridge

- Insert the narrow end of the cartridge into the inhaler.
- Place the inhaler on a firm surface and push down firmly until it clicks into place.

3. Replace clear base

- Put the clear base back into place until it clicks.
- Do not remove the clear base or the cartridge after it has been put together.

4. Turn

- Keep the cap closed.
- Turn the clear base in the direction of the arrows on the label until it clicks (half a turn).

5. Open

- Open the cap until it snaps fully open.

6. Press

- Point the inhaler toward the ground.
- Press the dose-release button.
- Close the cap.
- If you do not see a mist, repeat steps 4 to 6 until a mist is seen.
- After a mist is seen, repeat steps 4 to 6 three more times.
- After complete preparation of your inhaler, it will be ready to deliver the number of puffs on the label.

Daily use (T O P)

Turn

- Keep the cap closed.
- Turn the clear base in the direction of the arrows on the label until it clicks (half a turn).

Open

- Open the cap until it snaps fully open.

Press

- Breathe out slowly and fully.
- Close your lips around the mouthpiece without covering the air vents.
- Point the inhaler to the back of your throat.
- While taking a slow, deep breath through your mouth, Press the dose-release button and continue to breathe in.
- Hold your breath for 10 seconds or for as long as comfortable.
- Close the cap until you use your inhaler again.

Answers to Common Questions

It is difficult to insert the cartridge deep enough:

Did you accidentally turn the clear base before inserting the cartridge? Open the cap, press the dose-release button, then insert the cartridge.

Did you insert the cartridge with the wide end first? Insert the cartridge with the narrow end first.

I cannot press the dose-release button:

Did you turn the clear base? If not, turn the clear base in a continuous movement until it clicks (half a turn).

Is the dose indicator on the COMBIVENT RESPIMAT pointing to zero? The COMBIVENT RESPIMAT inhaler is locked after 120 puffs (120 doses). If you have a sample, the COMBIVENT RESPIMAT inhaler is locked after 60 puffs (60 doses). Prepare and use your new COMBIVENT RESPIMAT inhaler.

I cannot turn the clear base:

Did you turn the clear base already? If the clear base has already been turned, follow steps “Open” and “Press” under “Daily use” to get your medicine.

Is the dose indicator on the COMBIVENT RESPIMAT pointing to zero? The COMBIVENT RESPIMAT inhaler is locked after 120 puffs (120 doses). If you have a sample, the COMBIVENT RESPIMAT inhaler is locked after 60 puffs (60 doses). Prepare and use your new COMBIVENT RESPIMAT inhaler.

The dose indicator on the COMBIVENT RESPIMAT reaches zero too soon:

Did you use COMBIVENT RESPIMAT as indicated (1 puff four times daily)? COMBIVENT RESPIMAT will deliver 120 puffs and last 30 days if used at 1 puff four times daily. If you have a sample, COMBIVENT RESPIMAT will deliver 60 puffs and last 15 days if used at 1 puff four times daily.

Did you turn the clear base before you inserted the cartridge? The dose indicator counts each turn of the clear base regardless whether a cartridge has been inserted or not.

Did you spray in the air often to check whether the COMBIVENT RESPIMAT is working? Once you have prepared COMBIVENT RESPIMAT, no test-spraying is required if used daily.

Did you insert the cartridge into a used COMBIVENT RESPIMAT? Always insert a new cartridge into a NEW COMBIVENT RESPIMAT.

My COMBIVENT RESPIMAT sprays automatically:

Was the cap open when you turned the clear base? Close the cap, then turn the clear base.

Did you press the dose-release button when turning the clear base? Close the cap, so the dose-release button is covered, then turn the clear base.

Did you stop when turning the clear base before it clicked? Turn the clear base in a continuous movement until it clicks (half a turn).

My COMBIVENT RESPIMAT doesn’t spray:

Did you insert a cartridge? If not, insert a cartridge.

Did you repeat Turn, Open, Press (TOP) less than three times after inserting the cartridge? Repeat Turn, Open, Press (TOP) three times after inserting the cartridge as shown in steps 4 to 6 under “Prepare for first use”.

Is the dose indicator on the COMBIVENT RESPIMAT pointing to 0 (zero)? You have used up all your medicine and the inhaler is locked.

For more information about COMBIVENT RESPIMAT including current prescribing information or a video demonstration on how to use COMBIVENT RESPIMAT, go to www.combivent.com, scan the code, or call Boehringer Ingelheim Pharmaceuticals, Inc. at 1-800-542-6257.

This Instructions for Use has been approved by the U.S. Food and Drug Administration.

Distributed by: Boehringer Ingelheim Pharmaceuticals, Inc., Ridgefield, CT 06877 USA

Licensed from: Boehringer Ingelheim International GmbH

RESPIMAT® is a registered trademark of and used under license from Boehringer Ingelheim International GmbH

COMBIVENT® is a registered trademark of and used under license from Boehringer Ingelheim Pharmaceuticals, Inc.

Copyright © 2025 Boehringer Ingelheim International GmbH

ALL RIGHTS RESERVED

Revised: February 2025

COL10574BB102025

PRINCIPAL DISPLAY PANEL - 20 mcg/100 mcg Carton

NDC 0597-0024-02

Combivent® Respimat®
(ipratropium bromide and albuterol
inhalation spray)

20 mcg/100 mcg per actuation*

FOR ORAL INHALATION ONLY

Rx only

4 Grams
120 Metered Doses

Boehringer
Ingelheim